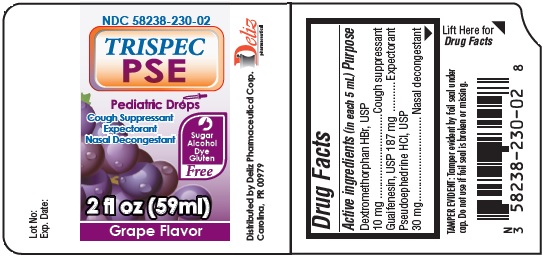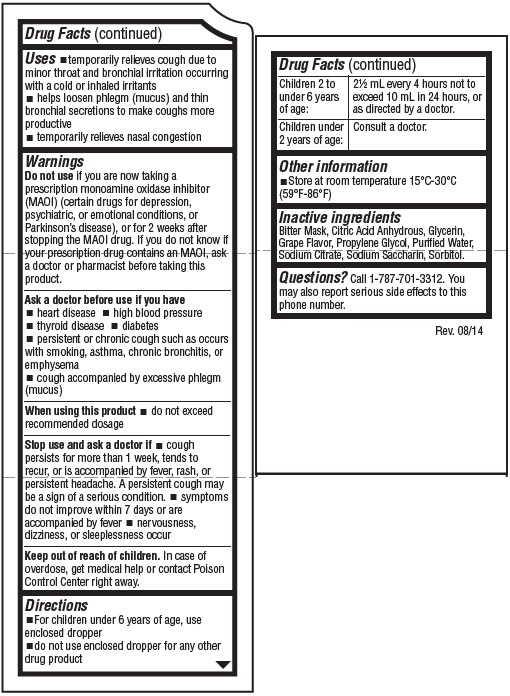 DRUG LABEL: TRISPEC PSE Pediatric Drops Cough Suppressant Expectorant Nasal Decongestant GRAPE Flavor
NDC: 58238-230 | Form: LIQUID
Manufacturer: Deliz Pharmaceutical Corp
Category: otc | Type: HUMAN OTC DRUG LABEL
Date: 20150828

ACTIVE INGREDIENTS: DEXTROMETHORPHAN HYDROBROMIDE 10 mg/5 mL; GUAIFENESIN 187 mg/5 mL; PSEUDOEPHEDRINE HYDROCHLORIDE 30 mg/5 mL
INACTIVE INGREDIENTS: ANHYDROUS CITRIC ACID; SODIUM CITRATE; GLYCERIN; SACCHARIN SODIUM; PROPYLENE GLYCOL; WATER; SORBITOL

TRISPEC PSE Pediatric Drops Cough Suppressant Expectorant Nasal Decongestant GRAPE Flavor

Active ingredients (in each 5 mL)

Dextromethorphan HBr, USP 10 mg
Guaifenesin, USP 187 mg
Pseudoephedrine HCl, USP 30 mg

Purpose

Cough suppressant
Expectorant
Nasal decongestant

Uses

- temporarily relieves cough due to minor throat and bronchial irritation occuring with a cold or inhaled irritants
- helps loosen phlegm (mucus) and thin bronchial secretions to make coughs more productive
- temporarily relieves nasal congestion

Warnings

Do not use

if you are now taking a prescription monoamine oxidase inhibitor (MAOI) (certain drugs for depression, psychiatric, or emotional conditions, or Parkinson’s disease), or for 2 weeks after stopping the MAOI drug. If you do not know if your prescription drug contains an MAOI, ask a doctor or pharmacist before taking this product.

Ask a doctor before use if you have

- heart disease
- high blood pressure
- thyroid disease
- diabetes
- persistent or chronic cough such as occurs with smoking, asthma, chronic bronchitis, or emphysema
- cough accompanied by excessive phlegm (mugus)

When using this product

- do not exceed recommended dosage

Stop use and ask a doctor if

- cough persists for more than 1 week, tends to recur, or is accompanied by fever, rash, or persistent headache. A persistent cough may be a sign of a serious condition.
- symptoms do not improve within 7 days or are acompanied by fever
- nervousness, dizziness, or sleeplessness occur

Keep out of reach of children.

In case of overdose, get medical help or contact a Poison Control Center right away.

Directions

- For children under 6 years of age, use enclosed dropper
- do not use enclosed dropper for any other drug product

Children 2 to under 6 years of age: | 2½ mL every 4 hours not to exceed 10 mL in 24 hours, or as directed by a doctor.
Children under 2 years of age: | Consult a doctor.

Other information

- Store at room temperature 15°C-30°C (59°F-86°F)

Inactive ingredients

Bitter Mask, Citric Acid Anhydrous, Glycerin, Grape Flavor, Propylene Glycol, Purified Water, Sodium Citrate, Sodium Saccharin, Sorbitol

Questions?

Call 1-787-701-3312. You may also report serious side effects to this phone number.